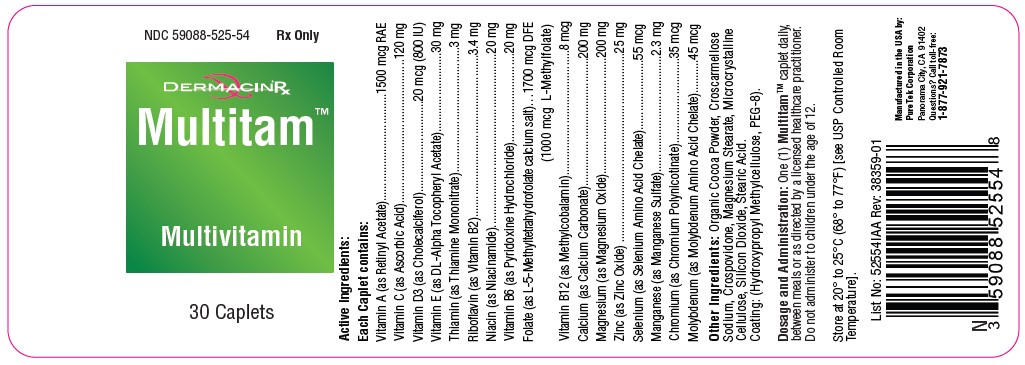 DRUG LABEL: Multitam
NDC: 59088-525 | Form: TABLET
Manufacturer: PureTek Corporation
Category: prescription | Type: HUMAN PRESCRIPTION DRUG LABEL
Date: 20241119

ACTIVE INGREDIENTS: .ALPHA.-TOCOPHEROL ACETATE, DL- 30 mg/1 1; MAGNESIUM OXIDE 200 mg/1 1; CHROMIUM NICOTINATE 35 ug/1 1; PYRIDOXINE HYDROCHLORIDE 20 mg/1 1; MOLYBDENUM 45 ug/1 1; SELENIUM 55 ug/1 1; CHOLECALCIFEROL 20 ug/1 1; RIBOFLAVIN 3.4 mg/1 1; NIACINAMIDE 20 mg/1 1; ASCORBIC ACID 120 mg/1 1; FOLIC ACID 1000 ug/1 1; CYANOCOBALAMIN 8 ug/1 1; CALCIUM CARBONATE 200 mg/1 1; VITAMIN A ACETATE 1500 ug/1 1; THIAMINE MONONITRATE 3 mg/1 1; ZINC OXIDE 25 mg/1 1; MANGANESE SULFATE 2.3 mg/1 1
INACTIVE INGREDIENTS: POLYETHYLENE GLYCOL 400; COCOA; CROSPOVIDONE; STEARIC ACID; MICROCRYSTALLINE CELLULOSE; CROSCARMELLOSE SODIUM; SILICON DIOXIDE; MAGNESIUM STEARATE

Multitam Multivitamin
Multivitamin
Rx Only
v2 Update color notes to "Beige speckled caplet" from "yellow to brown speckled caplet"

DESCRIPTION:

Active Ingredients:
Each Caplet contains:
Vitamin A (as Retinyl Acetate)...................................1500 mcg RAE
Vitamin C (as Ascorbic Acid)...............................................120 mg
Vitamin D3 (as Cholecalciferol)..............................20 mcg (800 IU)
Vitamin E (as DL-Alpha Tocopheryl Acetate)..........................30 mg
Thiamin (as Thiamine Mononitrate).........................................3 mg
Riboflavin (as Vitamin B2).....................................................3.4 mg
Niacin (as Niacinamide).........................................................20 mg
Vitamin B6 (as Pyridoxine Hydrochloride).............................20 mg
Folate (as L-5-Methyltetrahydrofolate calcium salt)…1700 mcg DFE
(1000 mcg L-Methylfolate)
Vitamin B12 (as Methylcobalamin).........................................8 mcg
Calcium (as Calcium Carbonate)..........................................200 mg
Magnesium (as Magnesium Oxide)......................................200 mg
Zinc (as Zinc Oxide) ..............................................................25 mg
Selenium (as Selenium Amino Acid Chelate).......................55 mcg
Manganese (as Manganese Sulfate)......................................2.3 mg
Chromium (as Chromium Polynicotinate)............................35 mcg
Molybdenum (as Molybdenum Amino Acid Chelate)...........45 mcg

Other Ingredients:
Organic cocoa powder, croscarmellose sodium, crospovidone, magnesium stearate, microcrystalline cellulose, silicon dioxide, stearic acid. Clear coating: (hydroxypropyl methylcellulose, PEG-8).

INDICATIONS:

Multitam™ is indicated to provide dietary support to men and women. Folate is effective in the treatment of megaloblastic anemias due to a deficiency of folate (as may be seen in tropical or nontropical sprue) and in anemias of nutritional origin, pregnancy, infancy, or childhood.

CONTRAINDICATIONS:

This product is contraindicated in patients with a known hypersensitivity to any of the ingredients.

WARNING:

Administration of folate alone is improper therapy for pernicious anemia and other megaloblastic anemias in which vitamin B12 is deficient.

PRECAUTIONS:

Folate in doses above 0.1 mg daily may obscure pernicious anemia, in that hematologic remission can occur while neurological manifestations remain progressive.
There is a potential danger in administering folate to patients with undiagnosed anemia, since folate may obscure the diagnosis of pernicious anemia by alleviating the hematologic manifestations of the disease while allowing the neurologic complications to progress. This may result in severe nervous system damage before the correct diagnosis is made. Adequate doses of vitamin B12 may
prevent, halt, or improve the neurologic changes caused by pernicious anemia.

The patient’s medical conditions and consumption of other drugs, herbs, and/or supplements should be considered.

For use on the order of a healthcare practitioner.
Call your doctor about side effects. To report side effects, call PureTek Corporation at 1-877-921-7873 or FDA at 1-800-FDA-1088 or www.fda.gov/medwatch.

Drug Interactions:

Multitam™ is not recommended for and should not be given to patients receiving levodopa because the action of levodopa is antagonized by pyridoxine. There is a possibility of increased bleeding due to pyridoxine interaction with anticoagulants (e.g., Aspirin, Heparin or Clopidogrel).

Adverse Reactions:

Allergic sensitization has been reported following both oral and parenteral administration of folate.
Adverse reactions have been reported with specific vitamins and minerals but generally at levels substantially higher than those contained herein. However, allergic and idiosyncratic reactions are possible at lower levels. Iron, even at the usual recommended levels, has been associated with gastrointestinal intolerance in some patients.

DOSAGE AND ADMINISTRATION:

One (1) Multitam™ caplet daily, between meals or as directed by a physician. Do not administer to children under the age of 12.

HOW SUPPLIED:

Multitam™ are beige speckled, oblong, coated caplets in bottles containing 30 caplets – NDC 59088-525-54. Dispense in a tight, light-resistant container as defined in the USP/NF with a child resistant closure.

Storage

Do not use if bottle seal is broken.
KEEP THIS AND ALL MEDICATIONS OUT OF THE REACH OF CHILDREN.
Store at controlled room temperature 20º-25ºC (68º-77ºF). [See USP].
Protect from light and moisture and avoid excessive heat.

To report a serious adverse event or to obtain product information, contact 877-921-7873.

Multitam

Manufactured in the USA by:

PureTek Corporation
Panorama City, CA 91402
Questions? Call toll-free:
1-877-921-7873